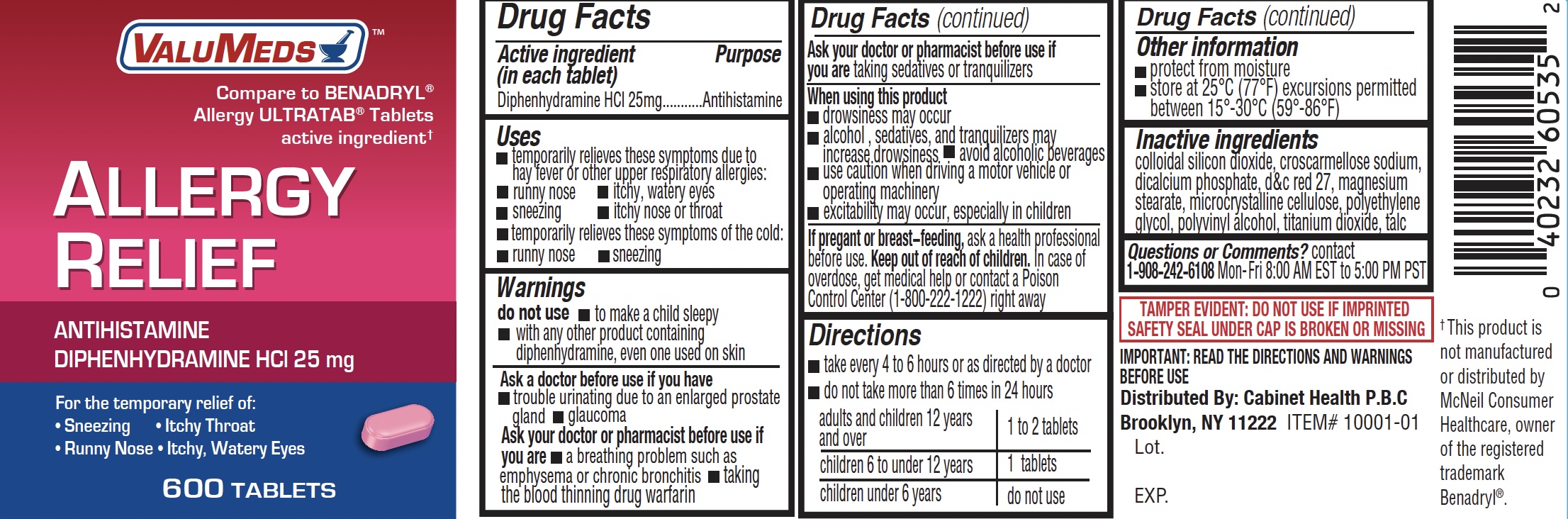 DRUG LABEL: Allergy Relief
NDC: 82725-1001 | Form: TABLET
Manufacturer: Cabinet Health, Inc
Category: otc | Type: HUMAN OTC DRUG LABEL
Date: 20250807

ACTIVE INGREDIENTS: DIPHENHYDRAMINE HYDROCHLORIDE 25 mg/1 1
INACTIVE INGREDIENTS: SILICON DIOXIDE; CROSCARMELLOSE SODIUM; D&C RED NO. 27; DIBASIC CALCIUM PHOSPHATE DIHYDRATE; HYPROMELLOSES; MAGNESIUM STEARATE; CELLULOSE, MICROCRYSTALLINE; POLYETHYLENE GLYCOL 400; POLYVINYL ALCOHOL; POLYSORBATE 80; TITANIUM DIOXIDE

DIPHENHYDRAMINE HCl Tablets, USP 25mg

Active Ingredient

(in each tablet)

Diphenhydramine HCl 25 mg

Purpose

Antihistamine

Uses

- temporarily relieves these symptoms due to hay fever or other upper respiratory allergies:
- runny nose
- sneezing
- itchy, watery eyes
- itchy nose or throat
- temporarily relieves these symptoms of the common cold:
- runny nose
- sneezing

Warnings

Do not use

- with any other product containing diphenhydramine, even one used on skin
- to make a child sleepy

Ask a doctor before use if you have

- trouble urinating due to an enlarged prostate gland
- glaucoma ? a breathing problem such as emphysema or chronic bronchitis

Ask a doctor or pharmacist before use if youaretaking sedatives or tranquilizers

When using this product

- marked drowsiness may occur
- avoid alcoholic drinks
- excitability may occur, especially in children ? alcohol, sedatives and tranquilizers may increase drowsiness
- be careful when driving a motor vehicle or operating machinery

If pregnant or breast-feeding;

ask a health professional before use

Keep out of reach of children.

In case of accidental overdose, contact a doctor or Poison Control Center immediately. Prompt medical attention is critical for adults as well as for children even if you do not notice any signs or symptoms.
Do not exceed recommended dosage.

Directions

- take every 4 to 6 hours, not more than 6 doses in 24 hours
- Adults and children 12 years of age and older:1 or 2 tablets
- children 6 to under 12 years of age:1 tablet
- children 4 to under 6 years of age:do not use unless directed by a doctor
- children under 4 years of age:do not use

Other Information

- each tablet contains : calcium 20 mg
- store at controlled room temperature 20°-25°C (68°-77°F).
- read all product information before using.
- TAMPER EVIDENT: DO NOT USE IF IMPRINTED SAFETY SEAL UNDER CAP IS BROKEN OR MISSING.

Inactive Ingredients

Colloidal silicon Dioxide, Croscarmellose Sodium, Dicalcium Phosphate, D & C Red, Magnesium stearate, Microcrystalline cellulose, Polyvinyl alcohol, Titanium dioxide, Talc

Questions or Comments

1-908-242-6108 (Mon-Fri 8AM-5PM EST)

PACKAGE LABEL.PRINCIPAL DISPLAY PANEL

DIPHENHYDRAMINE HYDROCHLORIDE TABLET

, USP 25 MG

ANTIHISTAMINE

* This product is not manufactured or distributed by McNeil-Consumer Healthcare, owner of the registered trademark Benadryl� Allergy.

82725-1001-1